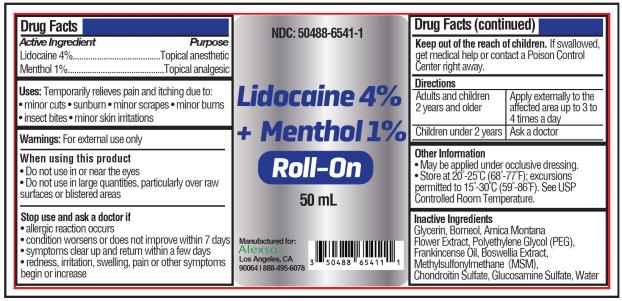 DRUG LABEL: Lidocaine 4 Percent and Menthol 1 Percent Roll-On
NDC: 50488-6541 | Form: LIQUID
Manufacturer: Alexso, Inc
Category: otc | Type: HUMAN OTC DRUG LABEL
Date: 20210223

ACTIVE INGREDIENTS: LIDOCAINE HYDROCHLORIDE 2 g/50 mL; MENTHOL 0.5 g/50 mL
INACTIVE INGREDIENTS: GLYCERIN; BORNEOL; ARNICA MONTANA FLOWER; POLYETHYLENE GLYCOL, UNSPECIFIED; FRANKINCENSE OIL; BOSWELLIA SACRA WHOLE; DIMETHYL SULFONE; CHONDROITIN SULFATE (BOVINE); GLUCOSAMINE SULFATE; WATER

Lidocaine and Menthol Roll-On

LIDOCAINE AND MENTHOL - Lidocaine 4% and Menthol 1% Roll-On
Alexso, Inc

Disclaimer: Most OTC drugs are not reviewed and approved by FDA, however they may be marketed if they comply with applicable regulations and policies. FDA has not evaluated whether this product complies.

----------

Lidocaine 4% and Menthol 1% Roll-On

Drug Facts

Active ingredient

Lidocaine 4%
Menthol 1%

Purpose

Topical anesthetic
Topical anesthetic

Uses

Temporarily relieves pain and itching due to:

- minor cuts
- sunburn
- minor scrapes
- minor burns
- insect bites
- minor skin irritations

Warnings

For external use only.

When using this product

- do not use in or near the eyes
- do not use in large quantities, particularly over raw surfaces or blistered areas
- do not apply to wounds or damaged skin
- do not bandage

Stop use and ask a doctor if

- allergic reaction occurs
- condition worsens or does not improve within 7 days
- symptoms clear up and return within a few days
- redness, irritation, swelling, pain or other symptoms begin or increase

Keep out of reach of children.

If swallowed, get medical help or contact a Poison Control Center right away.

Directions

adults and children 2 years and older | apply externally to the affected area up to 3 to 4 times a day
children under 2 years | do not use except under the advice and supervision of a physician

Other information

- May be applied under occlusive dressing.
- Store at 20-25°C (68-77°F); excursions permitted to 15-30°C (59-86°F). See USP Controlled Room Temperature.

Inactive ingredients

Glycerin, Borneol, Arnica Montana Flower Extract, Polyethylene Glycol (PEG), Frankincense Oil, Boswellia Extract, Methylsulfonylmethane (MSM), Chondroitin Sulfate, Glucosamine Sulfate, Water

PRINCIPAL DISPLAY PANEL

Lidocaine 4% and Menthol 1% Roll-On

NDC 50488-6541-1

50 mL

Manufactured for:
Alexso, Inc.
Los Angeles, CA 90064